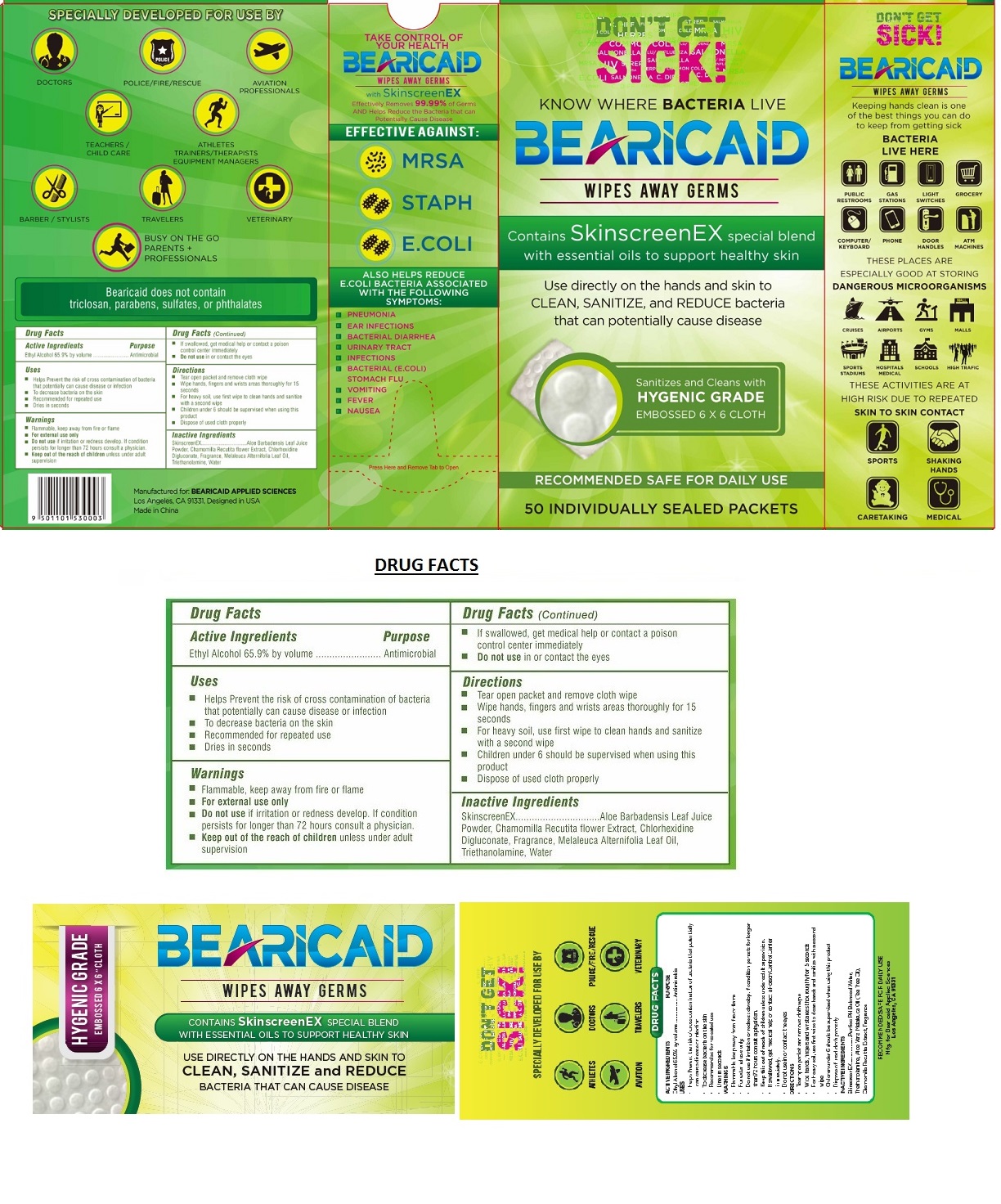 DRUG LABEL: BEARICAID ANTISEPTIC SKIN SANITIZING WIPES
NDC: 71504-659 | Form: CLOTH
Manufacturer: Knet Systems Corp.
Category: otc | Type: HUMAN OTC DRUG LABEL
Date: 20170609

ACTIVE INGREDIENTS: ALCOHOL 65.9 mL/100 mL
INACTIVE INGREDIENTS: ALOE VERA LEAF; CHAMOMILE; CHLORHEXIDINE GLUCONATE; TEA TREE OIL; TROLAMINE; WATER

BEARICAID ANTISEPTIC SKIN SANITIZING WIPES

Active Ingredients

Ethyl Alcohol 65.9% by volume

Purpose

Antimicrobial

Uses

• Helps Prevent the risk of cross contamination of bacteria that potentially can cause disease or infection

• To decrease bacteria on the skin

• Recommended for repeated use

• Dries in seconds

Warnings

• Flammable, keep away from fire or flame

• For external use only

• Do not use if irritation or redness develop. If condition persists for longer than 72 hours consult a physician.

KEEP OUT OF REACH OF CHILDREN

• Keep out of the reach of children unless under adult supervision

• If swallowed, get medical help or contact a poison control center immediately

• Do not use in or contact the eyes

Directions

• Tear open packet and remove cloth wipe

• Wipe hands, fingers and wrists areas thoroughly for 15 seconds

• For heavy soil, use first wipe to clean hands and sanitize with a second wipe

• Children under 6 should be supervised when using this product

• Dispose of used cloth properly

Inactive Ingredients

SkinscreenEX……………..Aloe Barbadensis Leaf Juice Powder, Chamomilla Recutita flower Extract, Chlorhexidine Digluconate, Fragrance, Melaleuca Alternifolia Leaf Oil, Triethanolamine, Water

Contains SkinscreenEx special blend with essential oils to support healthy skin

Use directly on the hands and skin to CLEAN, SANITIZE, and REDUCE bacteria that can potentially cause disease

Sanitizes and Cleans with HYGENIC GRADE EMBOSSED 6 X 6 CLOTH

RECOMMENDED SAFE FOR DAILY USE

50 INDIVIDUALLY SEALED PACKETS

Keeping hands clean is one of the best things you can do to keep from getting sick

Effectively Removes 99.99% of Germs AND Helps Reduce the Bacteria that can Potentially Cause Disease

EFFECTIVE AGAINST:
MRSA
STAPH
E.COLI

ALSO HELPS REDUCE E.COLI BACTERIA ASSOCIATED WITH THE FOLLOWING SYMPTOMS:

• PNEUMONIA
• EAR INFECTIONS
• BACTERIAL DIARRHEA
• URINARY TRACT
• INFECTIONS
• BACTERIAL (E.COLI) STOMACH FLU
• VOMITING
• FEVER
• NAUSEA

Bearicaid does not contain triclosan, parabens, sulfates, or phthalates

Manufactured for: BEARICAID APPLIED SCIENCES
Los Angeles, CA 91331, Designed in USA

Made in China